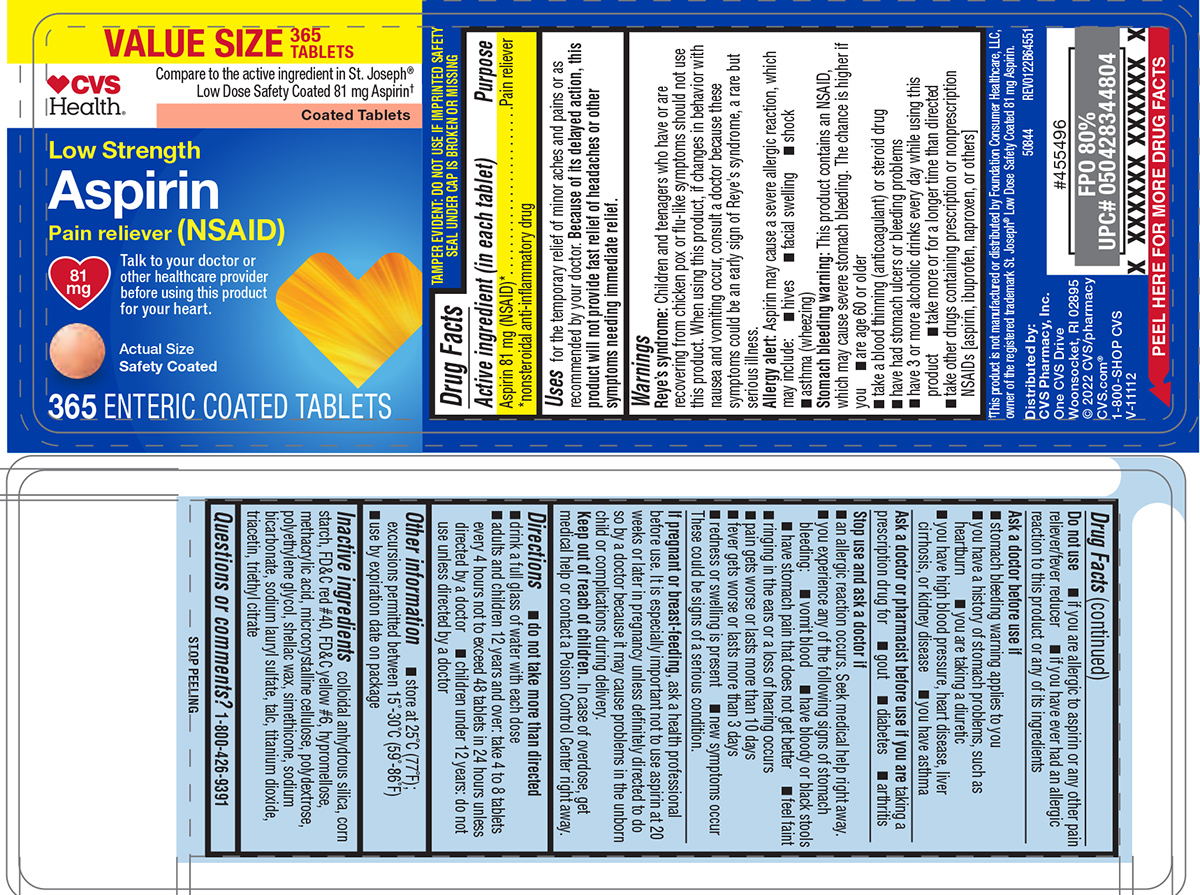 DRUG LABEL: ASPIRIN
NDC: 59779-945 | Form: TABLET, DELAYED RELEASE
Manufacturer: CVS Pharmacy
Category: otc | Type: HUMAN OTC DRUG LABEL
Date: 20260211

ACTIVE INGREDIENTS: ASPIRIN 81 mg/1 1
INACTIVE INGREDIENTS: SILICON DIOXIDE; STARCH, CORN; FD&C RED NO. 40; FD&C YELLOW NO. 6; HYPROMELLOSE, UNSPECIFIED; METHACRYLIC ACID; MICROCRYSTALLINE CELLULOSE; POLYDEXTROSE; POLYETHYLENE GLYCOL, UNSPECIFIED; SHELLAC; DIMETHICONE; WATER; SODIUM BICARBONATE; SODIUM LAURYL SULFATE; TALC; TITANIUM DIOXIDE; TRIACETIN; TRIETHYL CITRATE

CVS 44-645

Active ingredient (in each tablet)

Aspirin 81 mg (NSAID)*
*nonsteroidal anti-inflammatory drug

Purpose

Pain reliever

Uses

for the temporary relief of minor aches and pains or as recommended by your doctor. Because of its delayed action, this product will not provide fast relief of headaches or other symptoms needing immediate relief.

Warnings

Reye's syndrome: Children and teenagers who have or are recovering from chicken pox or flu-like symptoms should not use this product. When using this product, if changes in behavior with nausea and vomiting occur, consult a doctor because these symptoms could be an early sign of Reye's syndrome, a rare but serious illness.

Allergy alert: Aspirin may cause a severe allergic reaction, which may include:

- hives
- facial swelling
- shock
- asthma (wheezing)

Stomach bleeding warning: This product contains an NSAID, which may cause severe stomach bleeding. The chance is higher if you

- are age 60 or older
- take a blood thinning (anticoagulant) or steroid drug
- have had stomach ulcers or bleeding problems
- have 3 or more alcoholic drinks every day while using this product
- take more or for a longer time than directed
- take other drugs containing prescription or nonprescription NSAIDs [aspirin, ibuprofen, naproxen, or others]

Do not use

- if you are allergic to aspirin or any other pain reliever/fever reducer
- if you have ever had an allergic reaction to this product or any of its ingredients

Ask a doctor before use if

- stomach bleeding warning applies to you
- you have a history of stomach problems, such as heartburn
- you have high blood pressure, heart disease, liver cirrhosis, or kidney disease
- you have asthma
- you are taking a diuretic

Ask a doctor or pharmacist before use if you are

taking a prescription drug for

- gout
- diabetes
- arthritis

Stop use and ask a doctor if

- an allergic reaction occurs. Seek medical help right away.
- you experience any of the following signs of stomach bleeding:
  - vomit blood
  - have bloody or black stools
  - have stomach pain that does not get better
  - feel faint
- ringing in the ears or a loss of hearing occurs
- pain gets worse or lasts more than 10 days
- fever gets worse or lasts more than 3 days
- redness or swelling is present
- new symptoms occur

These could be signs of a serious condition.

If pregnant or breast-feeding,

ask a health professional before use. It is especially important not to use aspirin at 20 weeks or later in pregnancy unless definitely directed to do so by a doctor because it may cause problems in the unborn child or complications during delivery.

Keep out of reach of children.

In case of overdose, get medical help or contact a Poison Control Center right away.

Directions

- do not take more than directed
- drink a full glass of water with each dose
- adults and children 12 years and over: take 4 to 8 tablets every 4 hours not to exceed 48 tablets in 24 hours unless directed by a doctor
- children under 12 years: do not use unless directed by a doctor

Other information

- store at 25°C (77°F); excursions permitted between 15°-30°C (59°-86°F)
- use by expiration date on package

Inactive ingredients

colloidal anhydrous silica, corn starch, FD&C red #40, FD&C yellow #6, hypromellose, methacrylic acid, microcrystalline cellulose, polydextrose, polyethylene glycol, shellac wax, simethicone, sodium bicarbonate, sodium lauryl sulfate, talc, titanium dioxide, triacetin, triethyl citrate

Questions or comments?

1-800-426-9391

Principal Display Panel

VALUE SIZE
365
TABLETS

♥CVS
Health®

Compare to the active ingredient in St. Joseph®
Low Dose Safety Coated 81 mg Aspirin†

Coated Tablets

Low Strength
Aspirin
Pain reliever (NSAID)

81
mg

Talk to your doctor or
other healthcare provider
before using this product
for your heart.

Actual Size
Safety Coated

365 ENTERIC COATED TABLETS

TAMPER EVIDENT: DO NOT USE IF IMPRINTED SAFETY
SEAL UNDER CAP IS BROKEN OR MISSING

†This product is not manufactured or distributed by Foundation Consumer Healthcare, LLC,
owner of the registered trademark St. Joseph® Low Dose Safety Coated 81 mg Aspirin.

Distributed by:
CVS Pharmacy, Inc.
One CVS Drive
Woonsocket, RI 02895
© 2022 CVS/pharmacy
CVS.com® 1-800-SHOP CVS
V-11112

50844 REV0122B64551

CVS 44-645